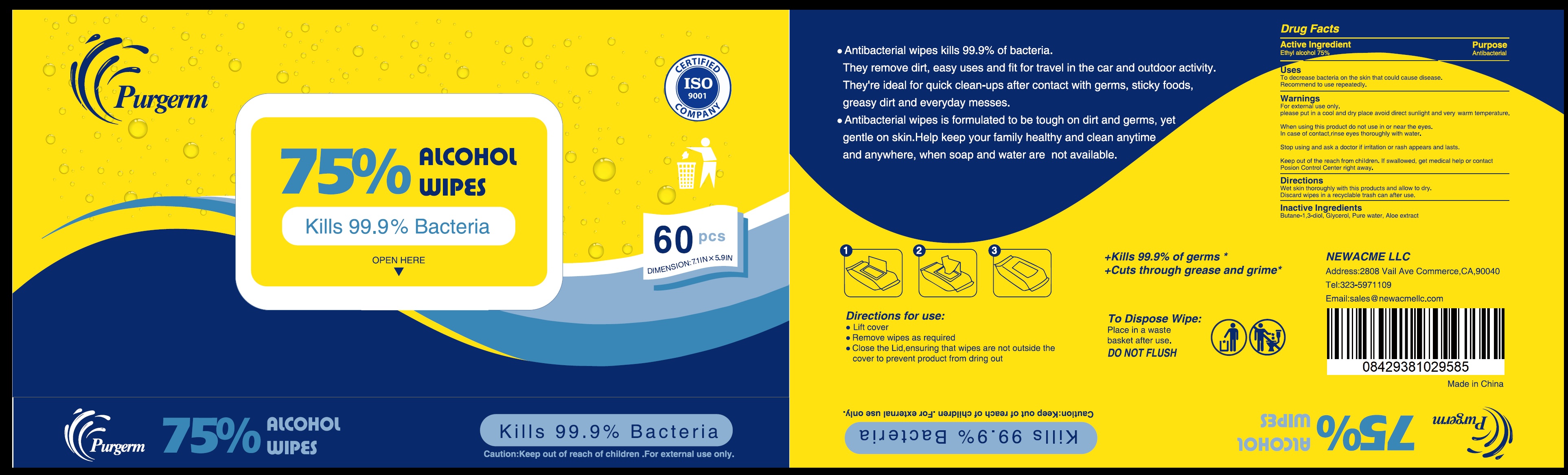 DRUG LABEL: 75 Alcohol Wipes
NDC: 74341-019 | Form: CLOTH
Manufacturer: Newacme LLC
Category: otc | Type: HUMAN OTC DRUG LABEL
Date: 20200721

ACTIVE INGREDIENTS: ALCOHOL 0.75 g/1 g
INACTIVE INGREDIENTS: BUTYLENE GLYCOL; GLYCERIN; WATER; ALOE VERA LEAF

75% Alcohol Wipes

Active Ingredient

Ethyl alcohol 75%

Purpose

Antibacterial

Uses

To decrease bacteria on the skin that could cause disease. Recommended to use repeatedly.

Warnings

For external use only.

please put in a cool and dry place avoid direct sunlight and very warm temperature.

When using this product

do not use in or near the eyes. In case of contact, rinse eyes thoroughly with water.

Stop use and ask a doctor

if irritation or rash appears and lasts.

Keep out of reach of children.

If swallowed, get medical help or contact Poison Control Center right away.

Directions

Wet skin thoroughly with this products and allow to dry. Discard wipes in a recyclable trash can after use.

Inactive Ingredients

Butane-1,3-diol, Glycerol, Pure water, Aloe extract